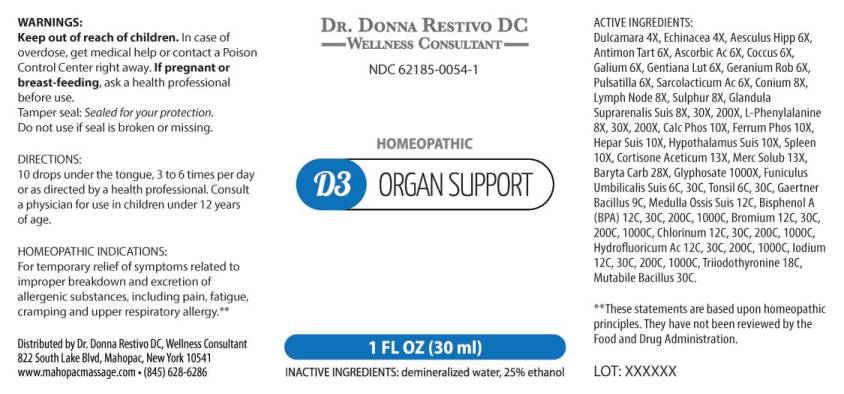 DRUG LABEL: D3 Organ Support
NDC: 62185-0054 | Form: LIQUID
Manufacturer: Dr. Donna Restivo DC
Category: homeopathic | Type: HUMAN OTC DRUG LABEL
Date: 20240118

ACTIVE INGREDIENTS: SOLANUM DULCAMARA TOP 4 [hp_X]/1 mL; ECHINACEA ANGUSTIFOLIA WHOLE 4 [hp_X]/1 mL; HORSE CHESTNUT 6 [hp_X]/1 mL; ANTIMONY POTASSIUM TARTRATE 6 [hp_X]/1 mL; ASCORBIC ACID 6 [hp_X]/1 mL; PROTORTONIA CACTI 6 [hp_X]/1 mL; GALIUM APARINE WHOLE 6 [hp_X]/1 mL; GENTIANA LUTEA ROOT 6 [hp_X]/1 mL; GERANIUM ROBERTIANUM WHOLE 6 [hp_X]/1 mL; PULSATILLA PRATENSIS WHOLE 6 [hp_X]/1 mL; LACTIC ACID, L- 6 [hp_X]/1 mL; CONIUM MACULATUM FLOWERING TOP 8 [hp_X]/1 mL; SUS SCROFA LYMPH 8 [hp_X]/1 mL; SULFUR 8 [hp_X]/1 mL; SUS SCROFA ADRENAL GLAND 8 [hp_X]/1 mL; PHENYLALANINE 8 [hp_X]/1 mL; TRIBASIC CALCIUM PHOSPHATE 10 [hp_X]/1 mL; FERROSOFERRIC PHOSPHATE 10 [hp_X]/1 mL; PORK LIVER 10 [hp_X]/1 mL; SUS SCROFA HYPOTHALAMUS 10 [hp_X]/1 mL; SUS SCROFA SPLEEN 10 [hp_X]/1 mL; CORTISONE ACETATE 13 [hp_X]/1 mL; MERCURIUS SOLUBILIS 13 [hp_X]/1 mL; BARIUM CARBONATE 28 [hp_X]/1 mL; GLYPHOSATE 1000 [hp_X]/1 mL; SUS SCROFA UMBILICAL CORD 6 [hp_C]/1 mL; SUS SCROFA TONSIL 6 [hp_C]/1 mL; SALMONELLA ENTERICA SUBSP. ENTERICA SEROVAR ENTERITIDIS 9 [hp_C]/1 mL; SUS SCROFA BONE MARROW 12 [hp_C]/1 mL; BISPHENOL A 12 [hp_C]/1 mL; BROMINE 12 [hp_C]/1 mL; CHLORINE 12 [hp_C]/1 mL; HYDROFLUORIC ACID 12 [hp_C]/1 mL; IODINE 12 [hp_C]/1 mL; LIOTHYRONINE 18 [hp_C]/1 mL; ESCHERICHIA COLI 30 [hp_C]/1 mL
INACTIVE INGREDIENTS: WATER; ALCOHOL

DRUG FACTS:

ACTIVE INGREDIENTS:

Dulcamara 4X, Echinacea (Angustifolia) 4X, Aesculus Hippocastanum 6X, Antimonium Tartaricum 6X, Ascorbicum Acidum 6X, Coccus Cacti 6X, Galium Aparine 6X, Gentiana Lutea 6X, Geranium Robertianum 6X, Pulsatilla (Pratensis) 6X, Sarcolacticum Acidum 6X, Conium Maculatum 8X, Lymph Node (Suis) 8X, Sulphur 8X, Glandula Suprarenalis Suis 8X, 30X,200, L-Phenylalanine 8X, 30X, 200X, Calcarea Phosphorica 10X, Ferrum Phosphoricum 10X, Hepar Suis 10X, Hypothalamus Suis 10X, Spleen (Suis) 10X, Cortisone Aceticum 13X, Mercurius Solubilis 13X, Baryta Carbonica 28X, Glyphosate 1000X, Funiculus Umbilicalis Suis 6C, 30C, Tonsil (Suis) 6C, 30C, Gaertner Bacillus (Bach) 9C, Medulla Ossis Suis 12C, Bisphenol A (BPA) 12C, 30C, 200C, 1000C, Bromium 12C, 30C, 200C, 1000C, Chlorinum 12C, 30C, 200C, 1000C, Hydrofluoricum Acidum 12C, 30C, 200C, 1000C, Iodium 12C, 30C, 200C, 1000C, Triiodothyronine 18C, Mutabile Bacillus (Bach) 30C.

HOMEOPATHIC INDICATIONS:

For temporary relief of symptoms related to improper breakdown and excretion of allergenic substances, including pain, fatigue, cramping and upper respiratory allergy.**

**These statements are based upon homeopathic principles. They have not been reviewed by the Food and Drug Administration.

WARNINGS:

Keep out of reach of children. In case of overdose, get medical help or contact a Poison Control Center right away.

If pregnant or breast-feeding, ask a health professional before use.

Tamper seal: Sealed for your protection.

Do not use if seal is broken or missing.

Keep out of reach of children. In case of overdose, get medical help or contact a Poison Control Center right away.

DIRECTIONS:

10 drops under the tongue, 3 to 6 times per day or as directed by a health professional. Consult a physician for use in children under 12 years of age.

HOMEOPATHIC INDICATIONS:

For temporary relief of symptoms related to improper breakdown and excretion of allergenic substances, including pain, fatigue, cramping and upper respiratory allergy.**

**These statements are based upon homeopathic principles. They have not been reviewed by the Food and Drug Administration.

INACTIVE INGREDIENTS:

demineralized water, 25% ethanol.

QUESTIONS:

Distributed by Dr. Donna Restivo DC, Wellness Consultant

822 South Lake Blvd. Mahopac, New York 10541

www.mahopacmassage.com • (845) 628-6286

PACKAGE LABEL DISPLAY:

DR. DONNA RESTIVO DC
WELLNESS CONSULTANT
NDC 62185-0054-1
HOMEOPATHIC
D3 ORGAN SUPPORT
1 FL OZ (30 ml)